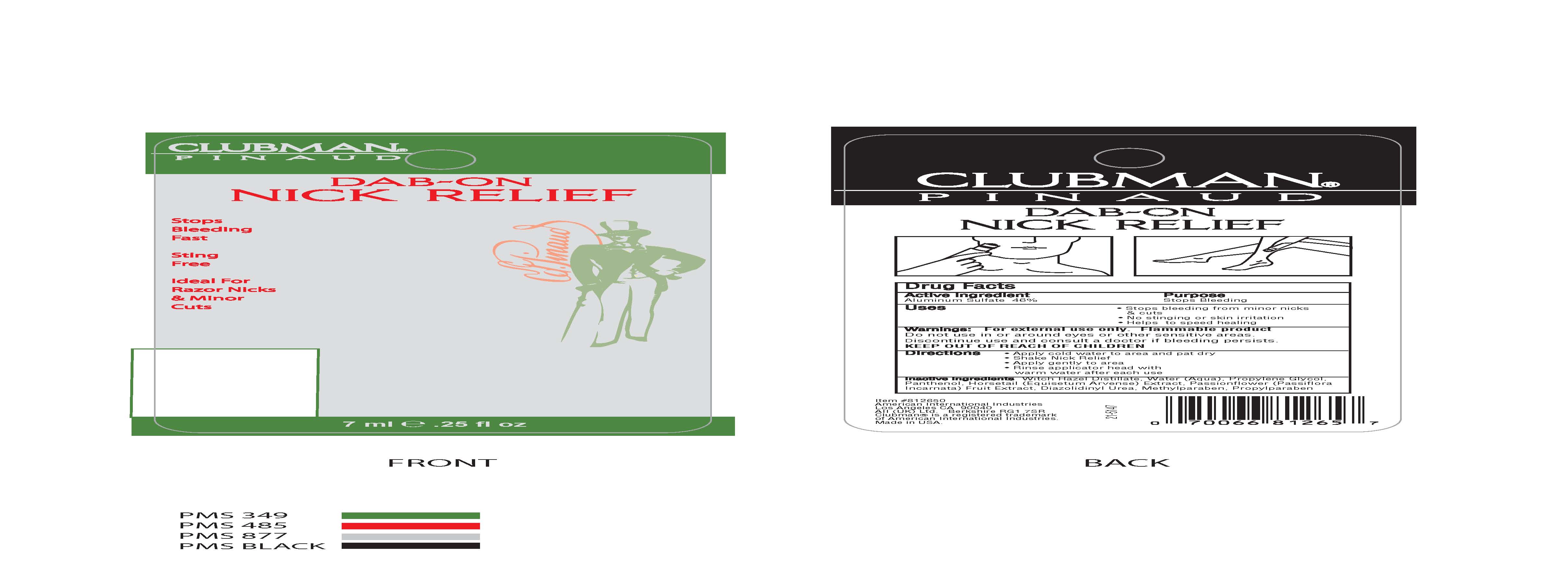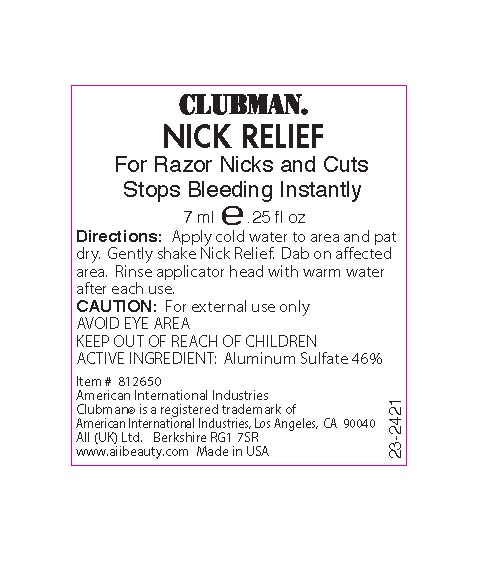 DRUG LABEL: NICK RELIEF
NDC: 57367-007 | Form: STICK
Manufacturer: 220 LABORATORIES INC
Category: otc | Type: HUMAN OTC DRUG LABEL
Date: 20100304

ACTIVE INGREDIENTS: ALUMINUM SULFATE 46 mg/1 mL
INACTIVE INGREDIENTS: WATER; WITCH HAZEL; PROPYLENE GLYCOL; DIAZOLIDINYLUREA; PANTHENOL; METHYLPARABEN; PROPYLPARABEN; MELISSA OFFICINALIS; MATRICARIA RECUTITA; ALOE VERA LEAF; GERANIUM EXTRACT; QUERCUS ALBA; ROSA CANINA FRUIT; SAGE; COMFREY; YARROW FLOWER; EAST INDIAN LEMONGRASS OIL; .ALPHA.-TOCOPHEROL ACETATE, D-

NICK RELIEF PACKAGING

BOXED WARNING

Warnings: For external use only. Flammable product.
Do not use in or around eyes or sensitive areas.
Discontinue use and consult a doctor if bleeding persists.

Directions:
Apply cold water to area and pat dry.
Shake Nick Relief.
Apply gently to area.
Rinse applicator head with warm water after each use.

Uses:
Stops bleeding from minor nicks and cuts.
No stinging or skin irritation.
Helps to speed healing.

Active Ingredient: Aluminum Sulfate 46%

INACTIVE INGREDIENT

Inactive ingredients: Witch Hazel Distillate, Water (Aqua), Propylene Glycol, Panthenol, Horsetail (Equisetum Arvense) Extract, Passionflower (Passiflora Incarnata) Fruit Extract, Diazolidinyl Urea, Methylparaben, Propylparaben

KEEP OUT OF REACH OF CHILDREN

Purpose: Stops bleeding

PACKAGE LABEL

Clubman

Nick Relief

For razor nicks and cuts

Stops Bleeding Instantly